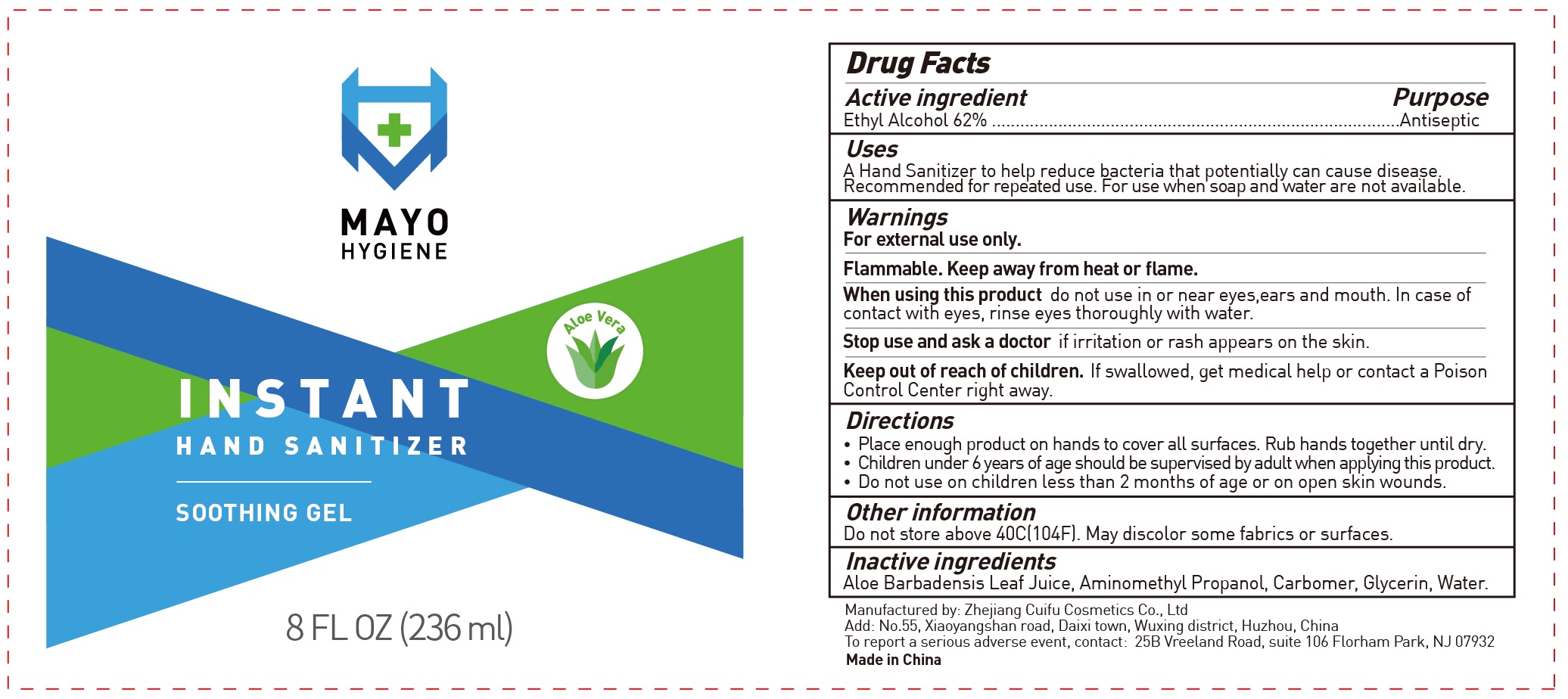 DRUG LABEL: Mayo Hygiene Instant Hand Sanitizer
NDC: 75809-000 | Form: GEL
Manufacturer: Zhejiang Cuifu Cosmetics Co., Ltd
Category: otc | Type: HUMAN OTC DRUG LABEL
Date: 20200629

ACTIVE INGREDIENTS: ALCOHOL 0.62 mL/1 mL
INACTIVE INGREDIENTS: ALOE VERA LEAF; AMINOMETHYLPROPANOL; CARBOMER HOMOPOLYMER, UNSPECIFIED TYPE; GLYCERIN; WATER

Mayo Hygiene Instant Hand Sanitizer

Active ingredient

Ethyl Alcohol 62%

Purpose

Antiseptic

Uses

A Hand Sanitizer to help reduce bacteria that potentially can cause disease. Recommended for repeated use. For use when soap and water are not available.

Warnings

For external use only.

Flammable. Keep away from heat or flame.

When using this product

do not use in or near eyes,ears and mouth. In case of contact with eyes, rinse eyes thoroughly with water.

Stop use and ask a doctor

if irritation or rash appears on the skin.

Keep out of reach of children.

If swallowed, get medical help or contact a Poison Control Center right away.

Directions

- Place enough product on hands to cover all surfaces. Rub hands together until dry.
- Children under 6 years of age should be supervised by adult when applying this product.
- Do not use on children less than 2 months of age or on open skin wounds.

Other information

Do not store above 40C(104F). May discolor some fabrics or surfaces.

Inactive ingredients

Aloe Barbadensis Leaf Juice, Aminomethyl Propanol, Carbomer, Glycerin, Water.